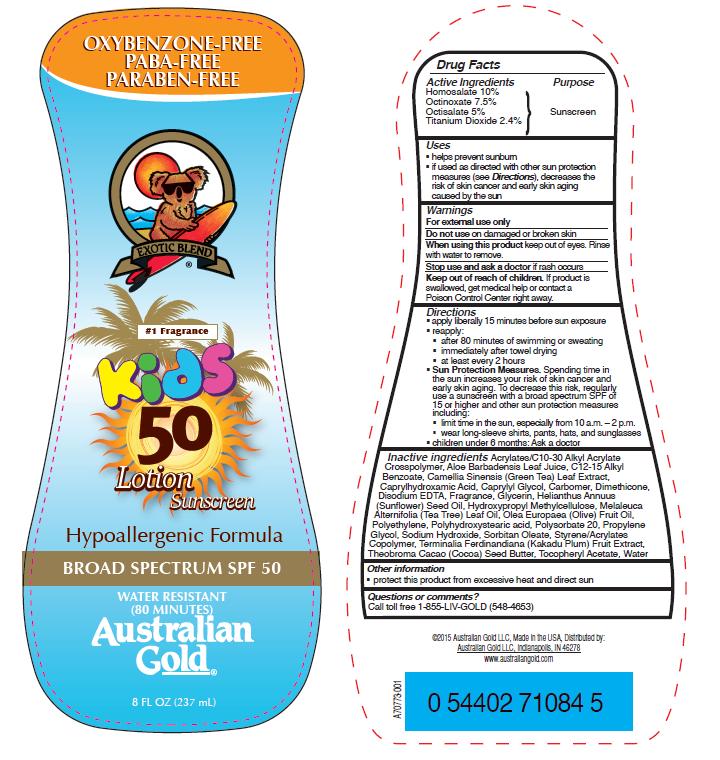 DRUG LABEL: Australian Gold
NDC: 58443-0200 | Form: LOTION
Manufacturer: Prime Enterprises Inc.
Category: otc | Type: HUMAN OTC DRUG LABEL
Date: 20200117

ACTIVE INGREDIENTS: TITANIUM DIOXIDE 24.5 mg/1 mL; HOMOSALATE 102 mg/1 mL; OCTISALATE 51 mg/1 mL; OCTINOXATE 76.5 mg/1 mL
INACTIVE INGREDIENTS: HYPROMELLOSES; OLIVE OIL; HIGH DENSITY POLYETHYLENE; POLYSORBATE 20; PROPYLENE GLYCOL; SORBITAN MONOOLEATE; CARBOMER HOMOPOLYMER TYPE C (ALLYL PENTAERYTHRITOL CROSSLINKED); GREEN TEA LEAF; ALKYL (C12-15) BENZOATE; SUNFLOWER OIL; ALOE VERA LEAF; (C10-C30)ALKYL METHACRYLATE ESTER; KAKADU PLUM; ALPHA-TOCOPHEROL ACETATE; CAPRYLYL GLYCOL; WATER; DIMETHICONE; POLYHYDROXYSTEARIC ACID (2300 MW); TEA TREE OIL; COCOA BUTTER; EDETATE DISODIUM; GLYCERIN; SODIUM HYDROXIDE; METHACRYLATE/METHOXY PEG-10 MALEATE/STYRENE COPOLYMER; CAPRYLHYDROXAMIC ACID

Australian Gold Kids SPF 50 Broad Spectrum Lotion Sunscreen

Active Ingredients

Homosalate 10%

Octinoxate 7.5%

Octisalate 5%

Titanium Dioxide 2.4%

Purpose

Sunscreen

Uses

- helps prevent sunburn
- if used as directed with other sun protection measures (see Directions), decreases the risk of skin cancer and early skin aging caused by the sun

WARNINGS

For external use only.

Do not use on damaged or broken skin

When using this product keep out of eyes. Rinse with water to remove.

Stop use and ask a doctor if rash occurs

Keep out of reach of children. If product is swallowed, get medical help or contact a Poison Control Center right away.

Directions

- apply liberally 15 minutes before sun exposure
- reapply:
- after 80 minutes of swimming or sweating
- immediately after towel drying
- at least every 2 hours
- Sun Protection Measures. Spending time in the sun increases your risk of skin cancer and early skin aging. To decrease this risk, regularly use a sunscreen with broad spectrum SPF of 15 or higher and other sun protection measures including:
- limit time in the sun, especially from 10 a.m. – 2 p.m.
- wear long-sleeve shirts, pants, hats, and sunglasses
- children under 6 months: Ask a doctor

INACTIVE INGREDIENT

Acrylates/C10-30 Alkyl Acrylate Crosspolymer, Aloe Barbadensis Leaf Juice, C12-15 Alkyl Benzoate, Camellia Sinensis (Green Tea) Leaf Extract, Caprylhydroxamic Acid, Caprylyl Glycol, Carbomer, Dimethicone, Disodium EDTA, Fragrance, Glycerin, Helianthus Annuus (Sunflower) Seed Oil, Hydroxypropyl Methylcellulose, Melaleuca Alternifolia (Tea Tree) Leaf Oil, Olea Europaea (Olive) Fruit Oil, Polyethylene, Polyhydroxystearic acid, Polysorbate 20, Propylene Glycol, Sodium Hydroxide, Sorbitan Oleate, Styrene/Acrylates Copolymer, Terminalia Ferdinandiana (Kakadu Plum) Fruit Extract, Theobroma Cacao (Cocoa) Seed Butter, Tocopheryl Acetate, Water

Other Information

- protect this product from excesive heat and direct sun

Questions or Comments?

Call toll free 1-855-LIV-GOLD (548-4653)